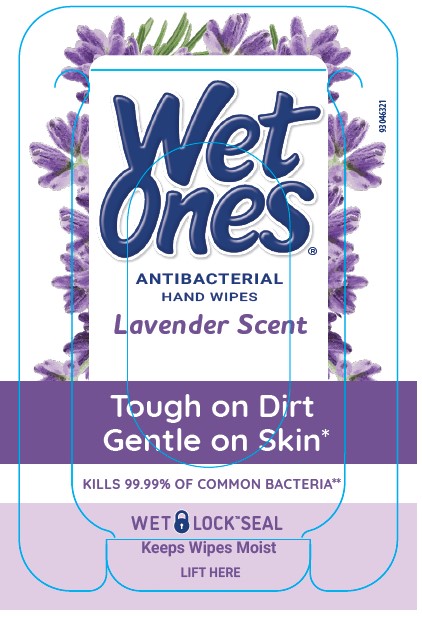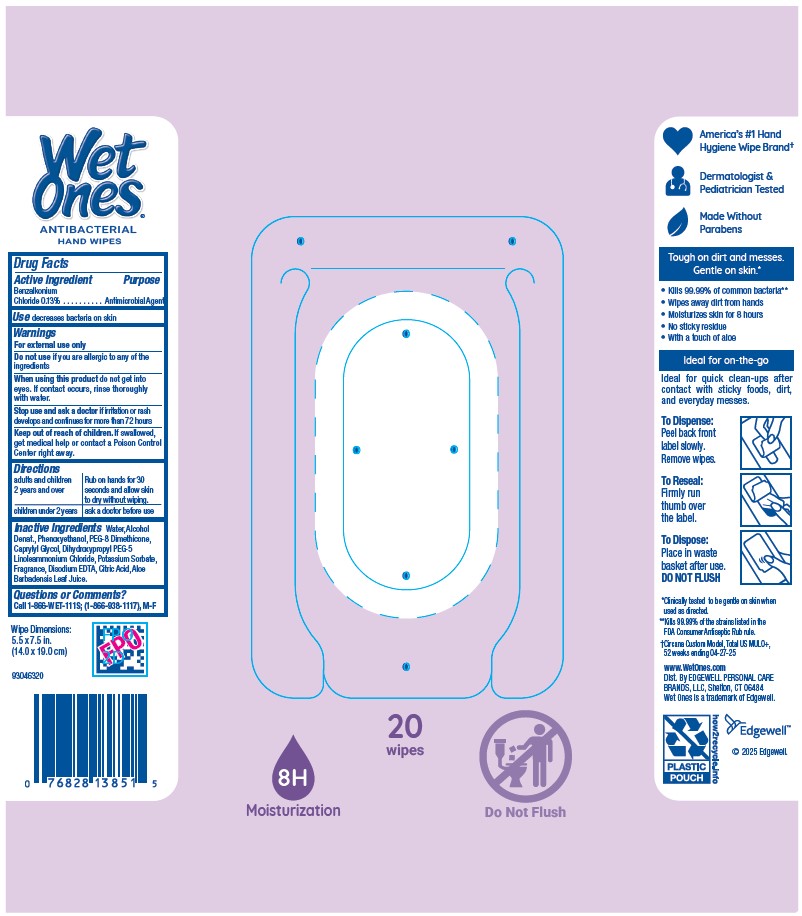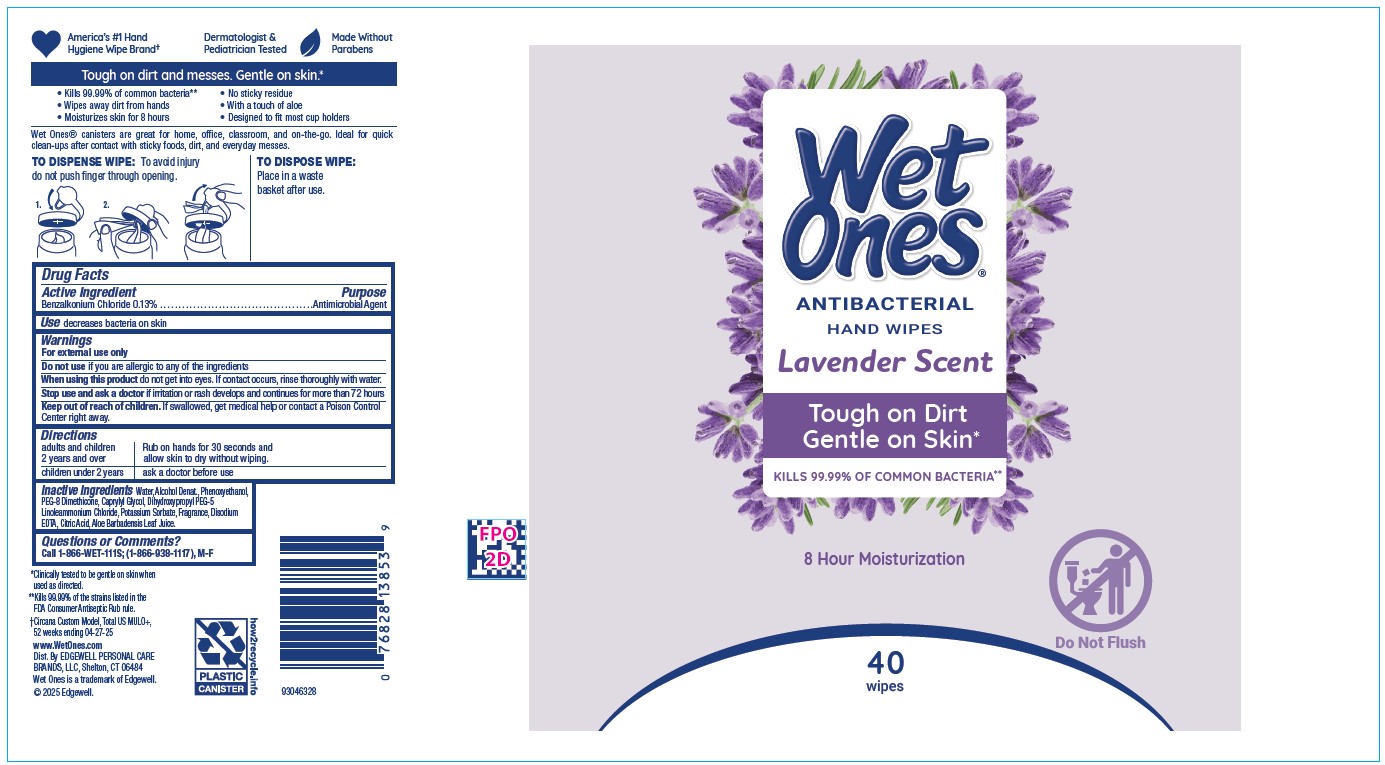 DRUG LABEL: Wet Ones Antibacterial Hand Wipes Lavender Scent
NDC: 63354-536 | Form: SWAB
Manufacturer: Edgewell Personal Care Brands LLC
Category: otc | Type: HUMAN OTC DRUG LABEL
Date: 20250917

ACTIVE INGREDIENTS: BENZALKONIUM CHLORIDE 0.13 g/100 g
INACTIVE INGREDIENTS: WATER; DEHYDRATED ALCOHOL; PEG-8 DIMETHICONE; CAPRYLYL GLYCOL; DIHYDROXYPROPYL PEG-5 LINOLEAMMONIUM CHLORIDE; EDETATE DISODIUM; CITRIC ACID MONOHYDRATE; ALOE VERA LEAF; PHENOXYETHANOL; POTASSIUM SORBATE

Active Ingredient

Benzalkonium Chloride 0.13%

Purpose

Antimicrobial Agent

Use

decreases bacteria on skin

Warnings

For external use only

Do not use

if you are allergic to any of the ingredients

When using this product

do not get into eyes. If contact occurs, rinse thoroughly with water.

Stop use and ask a doctor

if irritation or rash develops and continues for more than 72 hours

Keep out of reach of children.

If swallowed, get medical help or contact a Poison Control Center right away.

Directions

adults and children 2 years. Rub on hands for 30 seconds and allow skin to dry without wiping. Children under 2 years ask a doctor before use

Inactive Ingredients

Water, Alcohol Denat., Phenoxyethanol, PEG-8 Dimethicone, Caprylyl Glycol, Dihydroxypropyl PEG-5 Linoleammonium Chloride, Potassium Sorbate, Fragrance, Disodium EDTA, Citric Acid, Aloe Barbadensis Leaf Juice.

Questions or Comments?

Call 1-866-WET-111S; (1-866-938-1117), M-F

PRINCIPAL DISPLAY PANEL

Wet
Ones
ANTIBACTERIAL
HAND WIPES
Lavender Scent
Tough On Dirt
Gentle on Skin
KILLS 99.99% OF COMMON BACTERIA
WET LOCK SEAL
Keeps Wipes Moist
LIFT HERE

8H Moisturization
20
wipes
Do Not Flush

Wet
Ones
ANTIBACTERIAL
HAND WIPES
Lavender Scent
Tough On Dirt
Gentle on Skin
KILLS 99.99% OF COMMON BACTERIA
8 Hour Moisturization
Do Not Flush
40
wipes